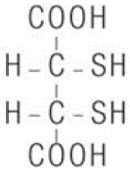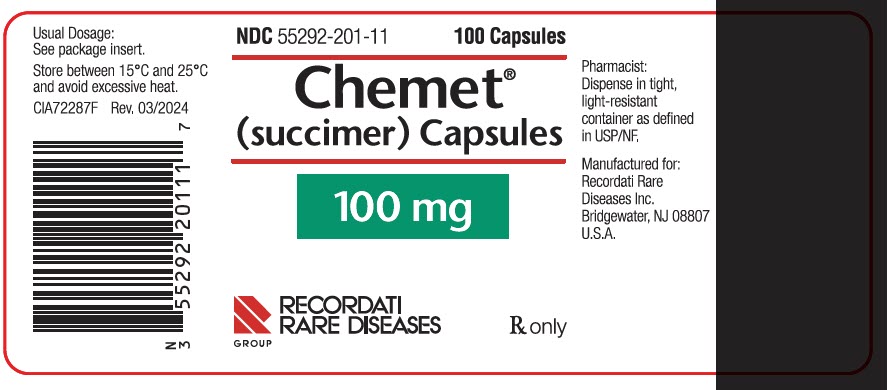 DRUG LABEL: Chemet
NDC: 55292-201 | Form: CAPSULE
Manufacturer: Recordati Rare Diseases, Inc.
Category: prescription | Type: HUMAN PRESCRIPTION DRUG LABEL
Date: 20250710

ACTIVE INGREDIENTS: SUCCIMER 100 mg/1 1
INACTIVE INGREDIENTS: SODIUM STARCH GLYCOLATE TYPE A POTATO; STARCH, CORN; POVIDONE, UNSPECIFIED; SUCROSE; GELATIN, UNSPECIFIED; FERRIC OXIDE RED; TITANIUM DIOXIDE

HIGHLIGHTS OF PRESCRIBING INFORMATION

These highlights do not include all the information needed to use CHEMET safely and effectively. See full prescribing information for CHEMET.
CHEMET (succimer capsules), for oral use
Initial U.S. Approval: 1982

1 INDICATIONS AND USAGE

CHEMET is a lead chelator indicated for the treatment of lead poisoning in pediatric patients aged 1 year and older with blood lead levels above 45 mcg/dL. (1)

Limitations of Use

- CHEMET is not indicated for prophylaxis of lead poisoning in a lead-containing environment. (1)
- CHEMET does not cross the blood-brain barrier and is not indicated to treat encephalopathy associated with lead toxicity. (1)

2 DOSAGE AND ADMINISTRATION

- See Full Prescribing Information for important pretreatment evaluations. (2.1)
- Ensure patients receiving CHEMET are adequately hydrated. (2.3)
- Administer CHEMET capsules whole when possible. (2.3)
- Pediatric patients who cannot swallow whole capsules: Sprinkle contents of capsule in food (or on a spoon followed by a drink). (2.3)
- Recommended Dosage: 10 mg/kg or 350 mg/m^2orally every 8 hours for five days followed by 10 mg/kg or 350 mg/m^2orally every 12 hours for an additional 14 days. (2.2)

3 DOSAGE FORMS AND STRENGTHS

Capsule: 100 mg (3)

4 CONTRAINDICATIONS

Patients with a history of hypersensitivity reaction to succimer. (4)

5 WARNINGS AND PRECAUTIONS

- Hypersensitivity and dermatologic reactions: Interrupt treatment if rash or mucocutaneous vesicular eruptions occur. (5.1)
- Neutropenia: Monitor complete blood counts, interrupt treatment for ANC below 1200/mcL, and monitor for infection. (5.2)
- Hepatic Toxicity: Monitor hepatic transaminases (ALT/AST); interrupt treatment if above 5 times ULN. (5.3)
- Embryo-Fetal Toxicity: May cause fetal harm when administered to a pregnant woman. (5.5)

6 ADVERSE REACTIONS

Most common adverse reactions (incidence ≥ 10%) in

- Pediatric patients: Digestive (nausea, vomiting, diarrhea, appetite loss, hemorrhoidal symptoms, metallic taste in mouth). (6.1)

To report SUSPECTED ADVERSE REACTIONS, contact Recordati Rare Diseases Inc. at 1-888-575-8344 or FDA at 1-800-FDA-1088 or www.fda.gov/medwatch.

7 DRUG INTERACTIONS

CHEMET may interfere with serum and urinary laboratory test. (7.1)

8 USE IN SPECIFIC POPULATIONS

Pregnancy: May cause fetal harm. (8.1)

Renal Impairment: Assess renal function. (8.6)

Hepatic Impairment: Assess hepatic function. (8.7)

FULL PRESCRIBING INFORMATION

1 INDICATIONS AND USAGE

CHEMET is indicated for the treatment of lead poisoning in pediatric patients aged 1 year and older with blood lead levels above 45 mcg/dL.

Limitations of Use

- CHEMET is not indicated for prophylaxis of lead poisoning in a lead-containing environment.
- CHEMET does not cross the blood-brain barrier and is not indicated to treat encephalopathy associated with lead toxicity.

2 DOSAGE AND ADMINISTRATION

2.1 Important Pretreatment Evaluations

- Identify the source of lead in the pediatric patient's environment and eliminate the source prior to beginning treatment with CHEMET.
- Assess the following before initiating treatment with CHEMET:
  - Blood lead concentration
  - Complete blood count (CBC) with differential and platelets [see Dosage and Administration (2.2), Warnings and Precautions (5.2)]
  - Ensure absolute neutrophil count (ANC) > 1500/mcL [see Dosage and Administration (2.2)]
  - Transaminases (AST/ALT) [see Warnings and Precautions (5.3)and Use in Specific Populations (8.6)]
  - Renal function with blood urea nitrogen (BUN), creatinine, urinary protein [see Use in Specific Populations (8.5)] .
- Patients who have previously received Edetate calcium disodium (CaNa2EDTA) with or without dimercaprol may receive CHEMET for subsequent treatment after an interval of four weeks.

2.2 Recommended Dosage

The recommended dosage of CHEMET for pediatric patients with lead poisoning is 10 mg/kg or 350 mg/m^2orally every 8 hours for five days followed by 10 mg/kg or 350 mg/m^2orally every 12 hours for an additional 14 days [see Table 1 CHEMET Pediatric Dosing Chart]. Initiation of therapy at higher doses is not recommended. The total treatment course consists of 19 days.

After discontinuation of CHEMET, elevated blood levels and associated symptoms may return rapidly because of redistribution of lead from bone stores to soft tissues and blood. Assess blood lead concentration after the completion of a 19 day course and every week until stable. Repeated courses may be administered after two weeks off treatment if blood lead concentrations remain elevated. A minimum of two weeks between treatment courses is recommended unless blood lead concentrations indicate the need for more prompt treatment.

Table 1. CHEMET Pediatric Dosing Chart
Weight in Kilograms (kg) | Dose (mg) | Number of Capsules
8 to15 kg | 100 mg | 1
16 to 23 kg | 200 mg | 2
24 to 34 kg | 300 mg | 3
35 to 44 kg | 400 mg | 4
>45 kg | 500 mg | 5

The safety of uninterrupted dosing longer than 3 weeks has not been established and is not recommended.

Dosage Modifications for Neutropenia

Monitor CBCs weekly.

If the absolute neutrophil count (ANC) is <1200/mcL interrupt CHEMET.

- Resume CHEMET when ANC has recovered to >1500/mcL (or the patient's baseline count).
- Immediately discontinue CHEMET for signs/symptoms of infection.
- Only rechallenge patients who developed neutropenia with CHEMET therapy if the benefit clearly outweighs the potential risk.

2.3 Preparation and Administration Instructions

Administer CHEMET capsules whole.

In pediatric patients who cannot swallow the capsules whole, separate the capsule and sprinkle the medicated beads on a small amount of soft food or put them in a spoon and follow with a fruit drink.

Ensure that all patients receiving CHEMET are adequately hydrated [see Use in Specific Populations (8.5), Pharmacokinetics (12.3)] .

3 DOSAGE FORMS AND STRENGTHS

Capsules: 100 mg, opaque white, imprinted black with "CHEMET 100".

4 CONTRAINDICATIONS

CHEMET is contraindicated in patients with a history of hypersensitivity reaction to succimer. Reactions have included mucocutaneous vesicular eruptions, urticaria, and angioedema [see Warnings and Precautions (5.1)] .

5 WARNINGS AND PRECAUTIONS

5.1 Hypersensitivity and Dermatologic Reactions

CHEMET can cause hypersensitivity reactions and dermatologic reactions.

Rash

Rash occurs in approximately 4% of patients treated with CHEMET. Interrupt treatment if rash occurs. Consider rechallenge if lead levels are high enough to warrant retreatment.

Hypersensitivity reactions including urticaria and angioedema have been reported on repeated administration of CHEMET [see Contraindications (4)].

Mucocutaneous Reactions

Mucocutaneous vesicular eruptions can occur with CHEMET use and may increase with each treatment course. Monitor patients requiring repeated CHEMET courses for the occurrence of mucocutaneous eruptions, including oral, urethral, and perianal. Interrupt treatment if mucocutaneous vesicular eruptions occur.

5.2 Neutropenia

Iron chelators, including CHEMET, can cause neutropenia. Monitoring of complete blood counts is recommended [see Dosage and Administration (2.2)] . Interrupt treatment if absolute neutrophil count (ANC) is <1200/mcL and interrupt treatment until recovery to above 1500/mcL (or the patient's baseline count). Only rechallenge patients who developed neutropenia with CHEMET therapy if the benefit clearly outweighs the potential risk. If rechallenge is attempted, monitor CBC more frequently.

Monitor for signs and symptoms of infection and immediately discontinue CHEMET if they develop.

5.3 Hepatic Toxicity

Elevated transaminases (ALT/AST) occurred in 6-10% of patients treated with CHEMET. Monitor serum AST and ALT at baseline and at least weekly during treatment. Monitor patients with a history of liver disease more frequently. Serum aminotransferase elevations above 5 times the upper limit of normal (if confirmed) should lead to dose reduction or temporary cessation.

5.4 Embryo-Fetal Toxicity

Based on findings from animal reproduction studies, CHEMET may cause fetal harm when administered to a pregnant woman. Advise females of reproductive potential to use an effective method of contraception during treatment with CHEMET and for 14 days after the final dose [see Use in Specific Populations (8.1, 8.3)] .

5.5 Laboratory Test Interference

CHEMET may interfere with serum and urinary laboratory tests [see Drug Interactions (7.1)] .

6 ADVERSE REACTIONS

The following clinically significant adverse reactions are described elsewhere in the labeling:

- Hypersensitivity and Dermatologic Reactions [see Warnings and Precautions (5.1)]
- Neutropenia [see Warnings and Precautions (5.2)]
- Hepatic Toxicity [see Warnings and Precautions (5.3)]

6.1 Clinical Trials Experience

Because clinical trials are conducted under widely varying conditions, adverse reaction rates observed in the clinical trials of a drug cannot be directly compared to rates in the clinical trials of another drug and may not reflect the rates observed in practice.

Table 2 presents the adverse reactions associated with Chemet in pediatric patients.

Table 2 Incidence of Adverse Reactions Associated with Chemet in Pediatric Patients
Body System: Adverse Reactions | Pediatric Patients (n=191)
Digestive [Nausea, vomiting, diarrhea, appetite loss, hemorrhoidal symptoms, metallic taste in mouth] | 12%
Body as a Whole [Back pain, abdominal cramps, stomach pains, head pain, rib pain, chills, flank pain, fever, flu-like symptoms, heavy head/tired, head cold, headache, moniliasis.] | 5%
Metabolic [Elevated ALT or AST, alkaline phosphatase, serum cholesterol.] | 4%
Respiratory [Sore throat, rhinorrhea, nasal congestion, cough.] | 4%
Skin [Papular rash, herpetic rash, rash, mucocutaneous eruptions, pruritis.] | 3%
Nervous [Drowsiness, dizziness, sensorimotor neuropathy, sleepiness, paresthesia.] | 1%
Special Senses [Cloudy film in eye, ears plugged, otitis media, eyes watery.] | 1%
Heme/Lymphatic [Neutropenia, increased platelet count, eosinophilia] | 1%

7 DRUG INTERACTIONS

7.1 Laboratory Test Interference

CHEMET may interfere with serum and urinary laboratory tests. In vitro studies have shown CHEMET to cause false positive results for ketones in urine using nitroprusside reagents and falsely decreased measurements of serum uric acid and creatinine phosphokinase (CPK).

7.2 Use with Other Chelation Therapies

Concomitant administration of CHEMET with other chelation therapy, such as CaNa2EDTA is not recommended.

8 USE IN SPECIFIC POPULATIONS

8.1 Pregnancy

Risk Summary

There are no studies with the use of CHEMET in pregnant women to inform drug-associated risks.

Administration of CHEMET to pregnant mice during organogenesis at dose exposure of 11-times the human exposure at the maximum recommended human dose (MRHD) of 700 mg based on body surface area (BSA) resulted in maternal toxicity and mortality and impaired reflex development in offspring (see Animal Data) . There are adverse effects on maternal and fetal outcomes associated with lead poisoning in pregnancy (see Clinical Considerations) . CHEMET should be used during pregnancy only if the potential benefit justifies the potential risk to the fetus.

The estimated background risk of major birth defects and miscarriage for the indicated population(s) is unknown. All pregnancies have a background risk of birth defect, loss, or other adverse outcomes. However, the background risk in the U.S general population of major birth defects is 2 to 4% and of miscarriage is 15 to 20% of clinically recognized pregnancies.

Clinical Considerations

Disease-Associated Maternal and/or Embryo/Fetal Risk

Lead exposure in pregnancy may increase the risk of gestational hypertension.

Lead crosses the placenta in amounts related to maternal plasma levels. Prenatal lead exposure may be associated with spontaneous abortion, preterm delivery, decreased birth weight, and impaired neurodevelopment.

Data

Animal Data

In embryo-fetal developmental studies, pregnant mice received subcutaneous succimer during the period of organogenesis at doses up to 1640 mg/kg/day (11-times the MRHD based on BSA) which resulted in both maternal and fetal toxicity.

In a developmental study in rats, dosing with succimer during the period of organogenesis resulted in maternal toxicity and deaths at the dose of 720 mg/kg/day (10-times the MRHD based on BSA) or more. The dose of 510 mg/kg/day (7-times the MRHD based on BSA) was the highest tolerable dose in pregnant rats. Impaired development of reflexes was noted in pups of dams receiving 720 mg/kg/day (10-times the MRHD based on BSA).

8.2 Lactation

Risk Summary

There are no data on the presence of succimer or its metabolite in either human or animal milk, the effects on the breastfed infant, or the effects on milk production. There are clinical considerations regarding lead in breastmilk (see Clinical Considerations) .

Clinical Considerations

When used for the treatment of lead poisoning, the amount of lead in breast milk may range from 0.6% to 3% of the maternal serum concentration. Females with confirmed blood lead levels ≥40 mcg/dL should not initiate breastfeeding; pumping and discarding breast milk is recommended until blood lead levels are <40 mcg/dL, at which point breastfeeding may resume. Calcium supplementation may reduce the amount of lead in breast milk.

8.3 Females and Males of Reproductive Potential

CHEMET may cause fetal harm when administered to a pregnant woman [see Use in Specific Populations (8.1)] .

Pregnancy Testing

Pregnancy testing is recommended for females of reproductive potential prior to treatment with CHEMET.

Contraception

Females

Advise females of reproductive potential to use effective contraception during treatment with CHEMET and for 14 days after the final dose.

8.4 Pediatric Use

The safety and effectiveness of CHEMET for the treatment of lead poisoning in patients with blood levels above 45 mcg/mL have been established in pediatric patients aged 1 year and older. The safety and effectiveness of CHEMET have not been established in pediatric patients younger than 1 year of age.

8.5 Renal Impairment

Assess renal function prior to and periodically during prolonged therapy. Adequately hydrate patients during therapy. Limited data suggests that succimer is dialyzable, but the lead chelates are not. Monitor patients with a history of renal impairment more frequently.

8.6 Hepatic Impairment

Assess hepatic function prior to and periodically during therapy. Monitor patients with a history of liver disease more frequently [see Warnings and Precautions (5.3)] .

10 OVERDOSAGE

Doses of 2300 mg/kg in the rat and 2400 mg/kg in the mouse produced ataxia, convulsions, labored respiration and frequently death. Limited data indicate that CHEMET is dialyzable. In case of acute overdosage, consider use of induction of vomiting or gastric lavage followed by administration of an activated charcoal slurry and appropriate supportive therapy.

11 DESCRIPTION

CHEMET (succimer) is an orally active, lead chelating agent. The chemical name for succimer is meso2, 3-dimercaptosuccinic acid (DMSA). Its empirical formula is C4H6O4S2and molecular weight is 182.2. The meso-structural formula is:

Succimer is a white crystalline powder with an unpleasant, characteristic mercaptan odor and taste.

Each CHEMET opaque white capsule for oral administration contains medicated beads with 100 mg of succimer and the following inactive ingredients: povidone, sodium starch glycolate, and sugar spheres. The capsule shell contains benzyl alcohol, butylparaben, edetate calcium disodium, gelatin, methylparaben, propylparaben, sodium lauryl sulfate, sodium propionate, titanium dioxide, and is imprinted with edible black ink.

12 CLINICAL PHARMACOLOGY

12.1 Mechanism of Action

Succimer is a lead chelator; it forms water soluble chelates and, consequently, increases the urinary excretion of lead.

12.2 Pharmacodynamics

Effect on Essential Minerals

In dose ranging studies performed in 18 men with blood lead levels of 44-96 mcg/dL, three groups of 6 patients received either 10, 6.7 or 3.3 mg/kg succimer orally every 8 hours for 5 days. After five days the mean blood lead levels of the three groups decreased 72.5%, 58.3% and 35.5% respectively. The mean urinary lead excretions in the initial 24 hours were 28.6, 18.6 and 12.3 times the pretreatment 24 hour urinary lead excretion. CHEMET had no significant effect on the urinary elimination of iron, calcium or magnesium. Zinc excretion doubled during treatment.

12.3 Pharmacokinetics

Absorption

Succimer achieved peak plasma concentrations at 1–2 hours.

Elimination

Metabolism

Approximately 90% of absorbed dose is metabolized to mixed succimer-cysteine disulfides. The majority of mixed disulfides consisted of succimer in disulfide linkages with two molecules of L-cysteine, the remaining disulfides contained one L-cysteine per succimer molecule.

Excretion

In a study performed in healthy adult volunteers, after a single dose of 14C-succimer at 16, 32, or 48 mg/kg, 49% of the radiolabeled dose was excreted on average: 39% in the feces, 9% in the urine and 1% as carbon dioxide from the lungs. The apparent elimination half-life of the radiolabeled material in the blood was about two days.

In other studies of healthy adult volunteers receiving a single oral dose of 10 mg/kg, approximately 25% of the administered dose was excreted in the urine with the peak blood level and urinary excretion occurring between two and four hours. Of the total amount of drug eliminated in the urine, approximately 90% was eliminated in altered form as mixed succimer-cysteine disulfides; the remaining 10% was eliminated unchanged.

13 NONCLINICAL TOXICOLOGY

13.1 Carcinogenesis, Mutagenesis, Impairment of Fertility

No carcinogenicity studies have been conducted with CHEMET. Succimer was not mutagenic in the Ames bacterial reverse mutation assay and in the mammalian cell forward gene mutation assay. Succimer did not show any adverse effects on fertility and reproductive performance in rats up to doses of 510 mg/kg/day in males and 100 mg/kg/day in females (7- and 11-times the MRHD based on BSA, respectively).

14 CLINICAL STUDIES

The efficacy of CHEMET in the treatment of lead poisoning in pediatric patients was established in a dose-ranging, actively controlled study of 15 pediatric patients aged 2 to 7 years with blood lead levels of 30-49 mcg/dL and positive CaNa2EDTA lead mobilization tests. Fifteen patients were assigned to a dose of 350 mg/m^2or 233 mg/m^2, or 116 mg/m^2(5 patients per group) orally every 8 hours for 5 days. Six control patients received 1000 mg/m^2/day CaNa2EDTA intravenously for 5 days. Following therapy, the mean blood lead levels decreased 78, 63, and 42% respectively in the three CHEMET treatment groups. The response of the 350 mg/m^2every 8 hours (10 mg/kg every 8 hours) group was significantly better than that of the other CHEMET dose level groups as well as that of the control group, whose mean blood lead level fell 48%. Although other dosing regimens were used in the study described, only 10 mg/kg or 350 mg/m^2orally every 8 hours for five days followed by 10 mg/kg or 350 mg/m^2orally every 12 hours for an additional 14 days is the recommended dosage.

Patients experienced a rebound in blood lead levels after discontinuation of CHEMET. In these studies, after treatment with a dose of 350 mg/m^2(10 mg/kg) every 8 hours for five days, the mean lead level rebounded and plateaued at 60-85% of pretreatment levels two weeks after therapy.

In an attempt to control rebound of blood lead levels, 19 pediatric patients, ages 1 to 7 years, with blood lead levels of 42-67 mcg/dL, were treated with 350 mg/m^2CHEMET every 8 hours for five days and then divided into three groups. One group was followed for two weeks with no further therapy, the second group was treated for two weeks with 350 mg/m^2daily, and the third with 350 mg/m^2every 12 hours. After the initial 5 days of therapy, the mean blood lead level in all subjects declined 61%. While the untreated group and the group treated with 350 mg/m^2daily experienced rebound during the ensuing two weeks, the group who received the 350 mg/m^2every 12 hours experienced no such rebound during the treatment period and less rebound following cessation of therapy.

In another study, ten pediatric patients, ages 21 to 72 months, with blood lead levels of 30-57 mcg/dL were treated with CHEMET 350 mg/m^2every eight hours for five days followed by an additional 19-22 days of therapy at a dose of 350 mg/m^2every 12 hours. The mean blood lead levels decreased and remained stable at under 15 mcg/dL during the extended dosing period.

In addition to the controlled studies, approximately 250 patients with lead poisoning have been treated with CHEMET either orally or parenterally in open U.S. and foreign studies.

16 HOW SUPPLIED/STORAGE AND HANDLING

Capsules: 100 mg of CHEMET (succimer), imprinted black with "CHEMET 100", in a bottle of 100 (NDC 55292-201-11).

STORAGE AND HANDLING

Store between 15°C and 25°C and avoid excessive heat.

Dispense in tight, light-resistant container.

17 PATIENT COUNSELING INFORMATION

- Advise caregivers and/or patients to maintain adequate fluid intake [see Dosage and Administration (2.3)].
- Advise caregivers and/or patients to contact their healthcare provider should a rash develop [see Warnings and Precautions (5.1)] .
- Advise caregivers and/or patients to contact their healthcare provider right away if signs/symptoms of infection develop [see Warnings and Precautions (5.2)] .
- Advise caregivers that in pediatric patients who cannot swallow the capsules whole, separate the capsule and sprinkle the medicated beads on a small amount of soft food or put them in a spoon and follow with a fruit drink [see Dosage and Administration (2.3)].

Manufactured for:
Recordati Rare Diseases Inc.
Bridgewater, NJ 08807

PRINCIPAL DISPLAY PANEL - 100 mg Capsule Bottle Label

NDC 55292-201-11
100 Capsules

Chemet®
(succimer) Capsules

100 mg

RECORDATI
RARE DISEASES
GROUP

Rx only